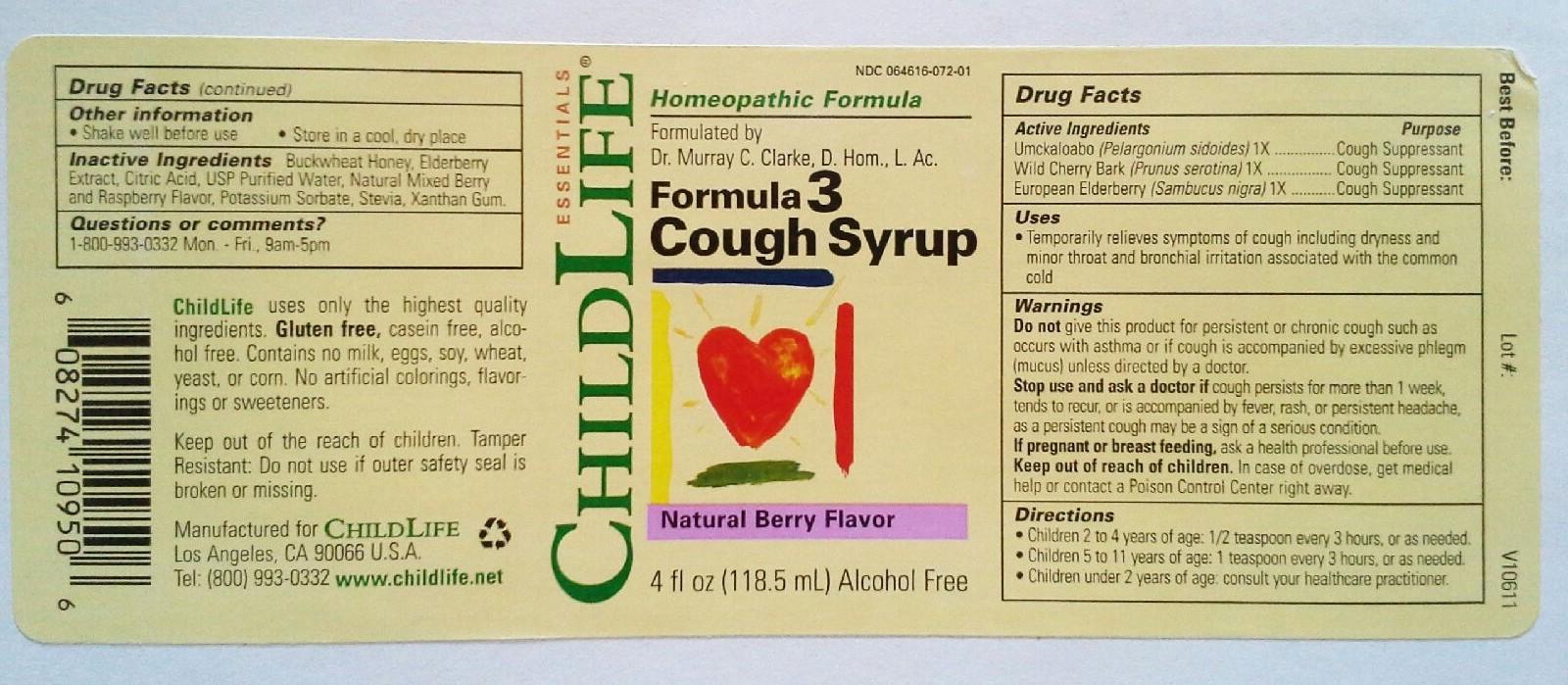 DRUG LABEL: Formula 3 Cough Syrup
NDC: 64616-072 | Form: LIQUID
Manufacturer: Vitality Works, Inc.
Category: homeopathic | Type: HUMAN OTC DRUG LABEL
Date: 20251217

ACTIVE INGREDIENTS: PELARGONIUM SIDOIDES ROOT 1 [hp_X]/1 mL; PRUNUS SEROTINA BARK 1 [hp_X]/1 mL; SAMBUCUS NIGRA FLOWER 1 [hp_X]/1 mL
INACTIVE INGREDIENTS: HONEY; AMERICAN ELDERBERRY; CITRIC ACID MONOHYDRATE; WATER; ALCOHOL; POTASSIUM SORBATE; STEVIA LEAF; XANTHAN GUM

Formula 3 Cough Syrup

Formula 3 Cough Syrup

Unckaloabo (Pelargonium sidoides) 1X

Wild Cherry Bark (Prunus serotina) 1X

European Elderberry (Sambucus nigra) 1X

Formula 3 Cough Syrup

Buckwheat Honey, Elderberry Extract, Citric Acid, USP Purified Water, Natural Mixed Berry and Raspberry Flavor, Potassium Sorbate, Stevia, Xanthan Gum

Formula 3 Cough Syrup

Do not give product for persistent or chronic cough such as occurs with asthma or if cough is accompanied excessive phlegm (mucus) unless directed by doctor. Stop use and ask a doctor if cough persists for more than 1 week, tends to recur, or is accompanied by fever, rash, or persistent headache, as a persistent cough may be a sign of a serious condition. If pregnant or breast feeding, ask a health professional before use. Keep out of reach of children. In case of overdose, get medical help or contact a Poison Control Center right away.

Formula 3 Cough Syrup

Keep out of reach of children. In case of overdose, get medical help or contact a Poison Control Center right away.

Formula 3 Cough Syrup

Temprarily relieves symptoms of cough including dryness and minor throat and bronchial irritation associated with the common cold.

Formula 3 Cough Syrup

Umckaloabo - Cough Suppressant

Wild Cherry Bark - Cough Suppressant

European Elderberry - Cough Suppressant

Formula 3 Cough Formula

- Children 2 to 4 years of age: 1/2 teaspoon every 3 hours, or as needed.

- Children 5 to 11 years of age: 1 teaspoon every 3 hours, or as needed.

Children under 2 years of age: Consult your healthcare practitioner